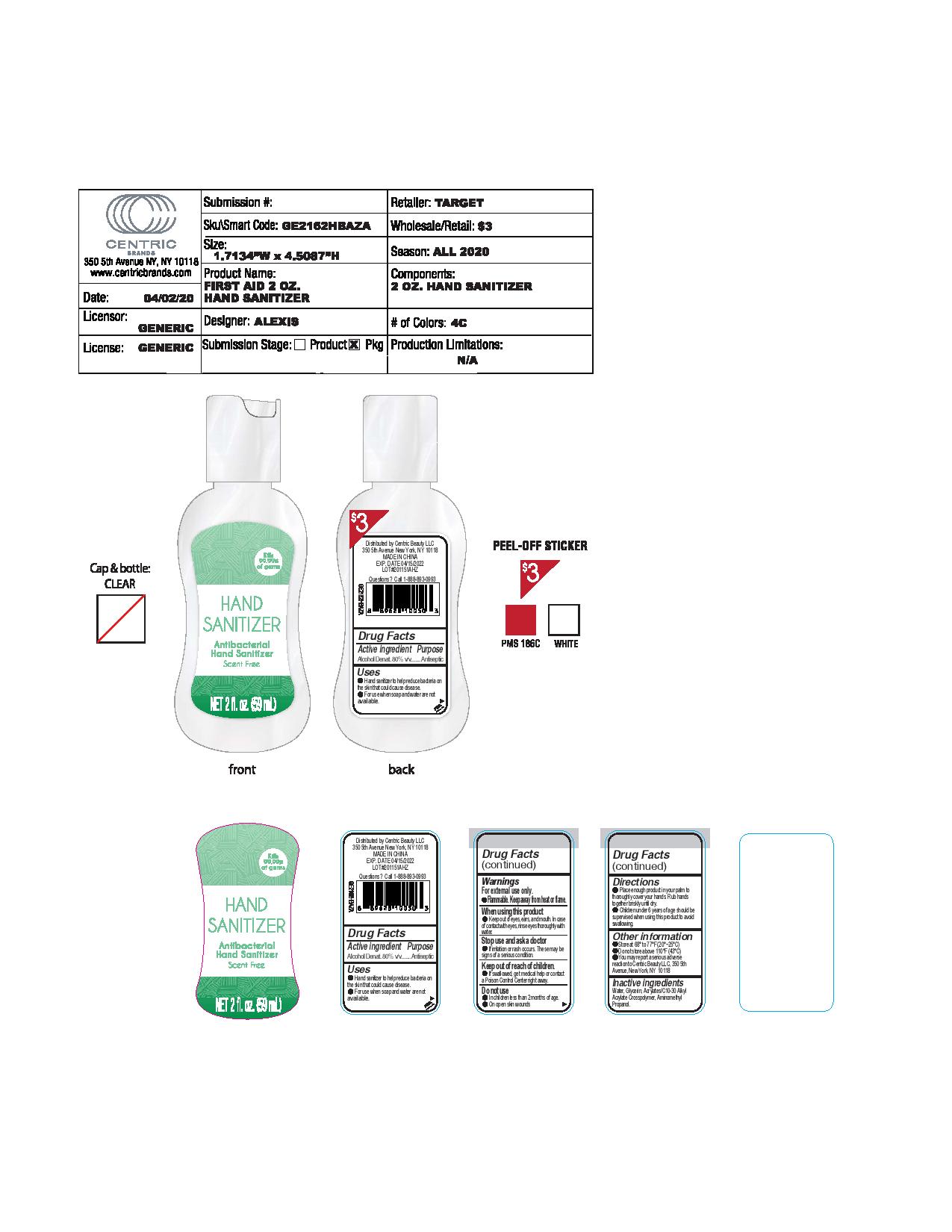 DRUG LABEL: Antibacterial Hand Sanitizer
NDC: 51522-003 | Form: GEL
Manufacturer: Gold Orient International Limited
Category: otc | Type: HUMAN OTC DRUG LABEL
Date: 20200420

ACTIVE INGREDIENTS: ALCOHOL 80 mL/100 mL
INACTIVE INGREDIENTS: WATER; CARBOMER COPOLYMER TYPE A (ALLYL PENTAERYTHRITOL CROSSLINKED); GLYCERIN; AMINOMETHYLPROPANOL

Antibacterial Hand Sanitizer

INDICATIONS AND USAGE

for hand washing to decrease bacteria on the skin only when water is not available.

Drug Facts Active Ingredients

Alcohol Denat. 80%

Purpose

Antiseptic

DOSAGE AND ADMINISTRATION

- Place enough product in your plam to thoroughly cover your hands. Rub hands together briskly until dry.
- Children under 6 years of age should be supervised when this product to avoid swallowing

Inactive Ingredients:

Water, Glycerin, Acrylates/C10-30 Alkyl Acrylate Crosspolymer, Aminomthyl Propanol

Warning

- For External Use Only.
- Flammable, keep away from heat or flame

When using this product

- Keep out of eyes, ears, and mouth. In case of contact with eyes thoroughly with water.

Stop use and ask a doctor

- if irritation or rash occurs. These may be signs of a serious condition.

Keep out of reach of children, if swallowed, get medical help or contact a Poison Control Center right away.

DO NOT USE

- In children less than 2 months of age.
- On open skin wounds

OTHER SAFETY INFORMATION

- Store at 68 to 77F (20-25C)
- Do not store above 100F (43C)
- You may report a serious advers reaction to Centric Beauty LLC, 350 5th Avenue, New York, NY 10118